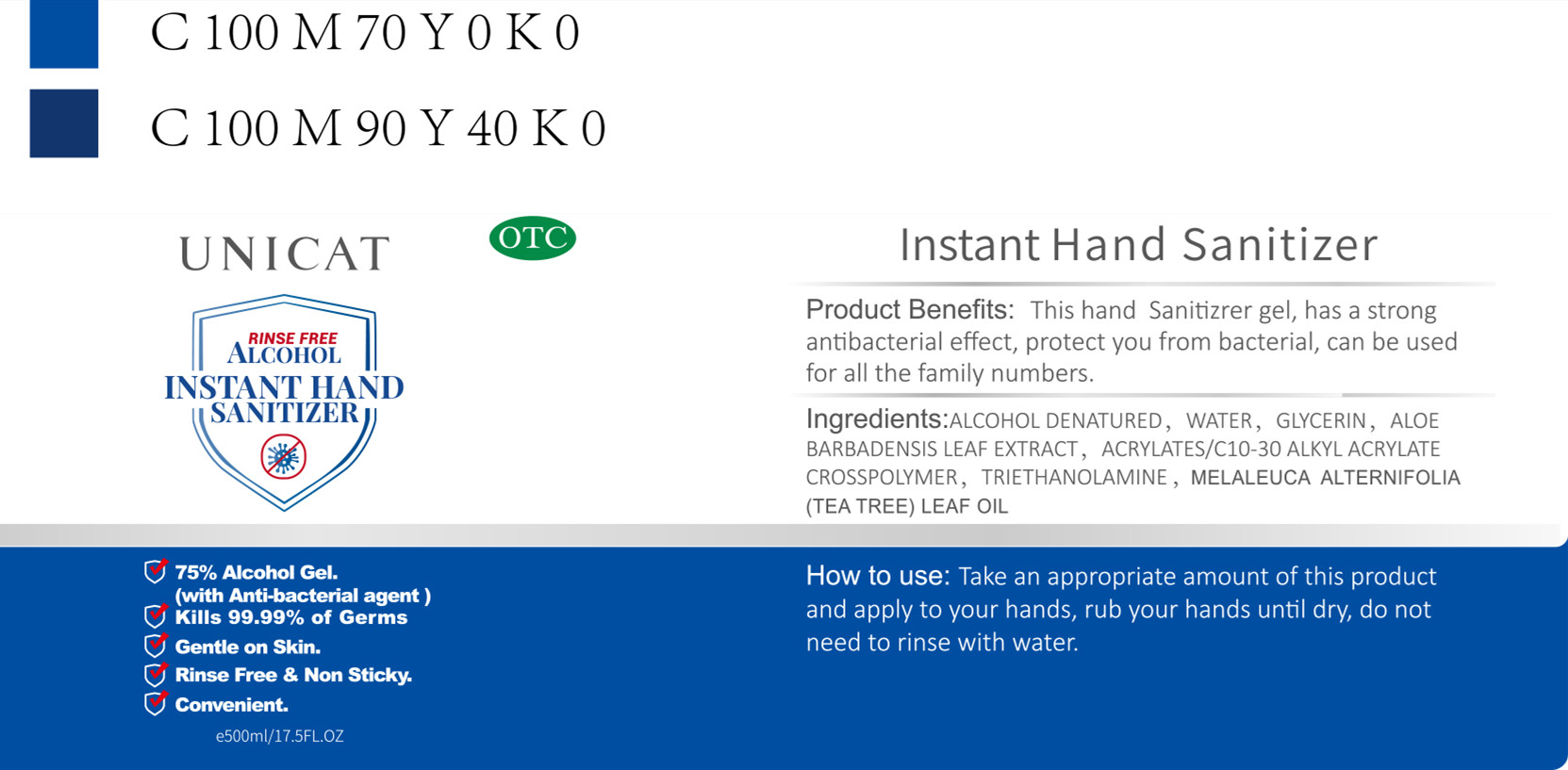 DRUG LABEL: Instant Hand Sanitizer
NDC: 55224-001 | Form: GEL
Manufacturer: DONGGUAN KE-YAN Bio-Chemical CO.,LTD
Category: otc | Type: HUMAN OTC DRUG LABEL
Date: 20200419

ACTIVE INGREDIENTS: ALCOHOL 375 mL/500 mL
INACTIVE INGREDIENTS: CARBOMER INTERPOLYMER TYPE A (ALLYL SUCROSE CROSSLINKED); MELALEUCA ALTERNIFOLIA LEAF; WATER; ALOE VERA LEAF; GLYCERIN

DOSAGE AND ADMINISTRATION

This product is for external use only. Store in a cool place, keep it away form fir.

INACTIVE INGREDIENT

WATER

GLYCERIN

ALOE BARBADENSIS

ACRYLATES/C10-30 ALKYL ACRYLATE CROSSPOLYMER

MELALEUCA ALTERNIFOLIA

INDICATIONS AND USAGE

Take an appropriate amount of this product and apply to your hands, rub your hands until dry, do not need to rinse with water.

ACTIVE INGREDIENT

ALCOHOL

keep out of children

PURPOSE

Disinfection
Sterilization
No Rinseing

WARNINGS

This product is for external use only. Store in a cool place, keep it away form fir. eIn case of contact with eyes, rinse thoroughly with water.